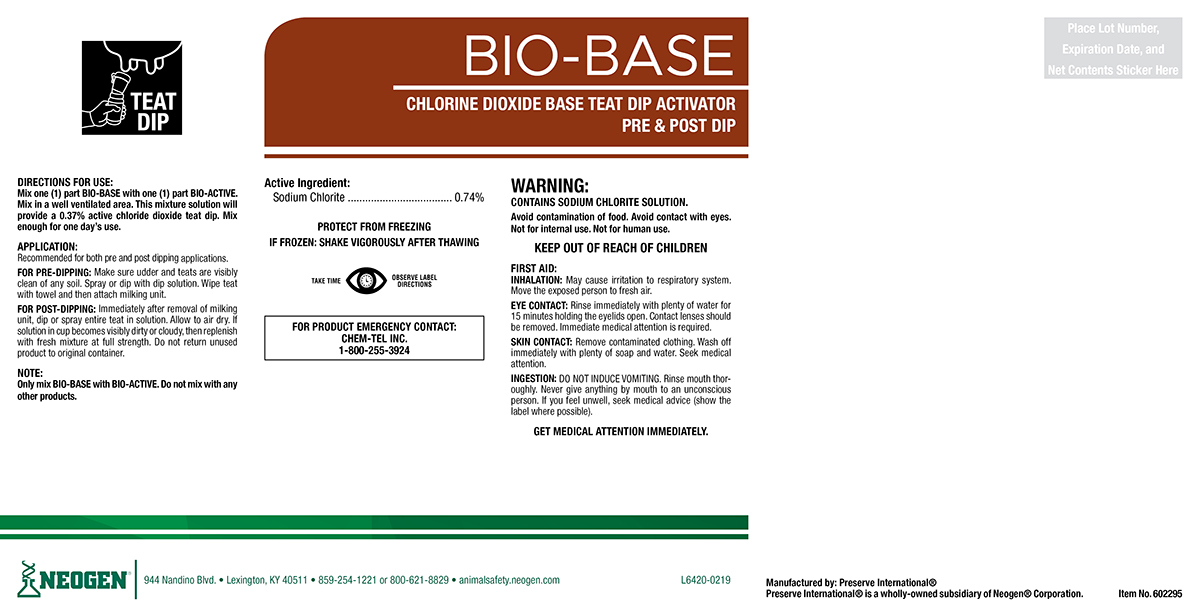 DRUG LABEL: Bio-Base
NDC: 60648-9013 | Form: SOLUTION
Manufacturer: Preserve International
Category: animal | Type: OTC ANIMAL DRUG LABEL
Date: 20190517

ACTIVE INGREDIENTS: SODIUM CHLORITE 7.51 g/1 L

BIO-BASE

DIRECTIONS FOR USE:

Mix one (1) part BIO-BASE with one (1) part BIO-ACTIVE. Mix in a well ventilated area. This mixture solution will provide a 0.37% active chlorine dioxide teat dip. Mix enough for one day's use.

APPLICATION:

Recommended for both pre and post dipping applications.

FOR PRE-DIPPING: Make sure udder and teats are visibly clean of any soil. Spray or dip with dip solution. Wipe teat with towel and then attach milking unit.

FOR POST-DIPPING: Immediately after removal of milking unit, dip or spray entire teat in solution. Allow to air dry. If solution in cup becomes visibly dirty or cloudy, then replenish with fresh mixture at full strength. Do not return unused product to original container.

NOTE:

Only mix BIO-BASE with BIO-ACTIVE. Do not mix with any other products.

WARNINGS AND PRECAUTIONS

PROTECT FROM FREEZING

IF FROZEN: SHAKE VIGOROUSLY AFTER THAWING

WARNINGS AND PRECAUTIONS

TAKE TIME OBSERVE LABEL DIRECTIONS

WARNING:

CONTAINS SODIUM CHLORITE SOLUTION

Avoid contamination of food. Avoid contact with eyes. Not for internal use. Not for human use.

KEEP OUT OF REACH OF CHILDREN

FIRST AID:

INHALATION: May cause irritation to respiratory system. Move the exposed person to fresh air.

EYE CONTACT: Rinse immediately with plenty of water for 15 minutes holding the eyelids open. Contact lenses should be removed. Immediate medical attention is required.

SKIN CONTACT: Remove contamianted clothing. Wash off immediately with plenty of soap and water. Seek medical attention.

INGESTION: DO NOT INDUCE VOMITING. Rinse mouth thoroughly. Never give anything by mouth to an unconscious person. If you feel unwell, seek medical advice (show the label where possible).
GET MEDICAL ATTENTION IMMEDIATELY.

FOR PRODUCT EMERGENCY CONTACT: Chem-Tel Inc. 1-800-255-3924

PACKAGE LABEL

BIO-BASE

CHLORINE DIOXIDE BASE TEAT DIP ACTIVATOR

PRE & POST DIP

Active Ingredients:

Sodium Chlorite..........................0.74%

Manufactured By: Preserve International®

Preserve International® is a wholly-owned subsidiary of Neogen® Corporation.

NEOGEN®

944 Nandino Blvd.

Lexington, KY 40511

859-254-1221 or 800-621-8829

animalsafety.neogen.com